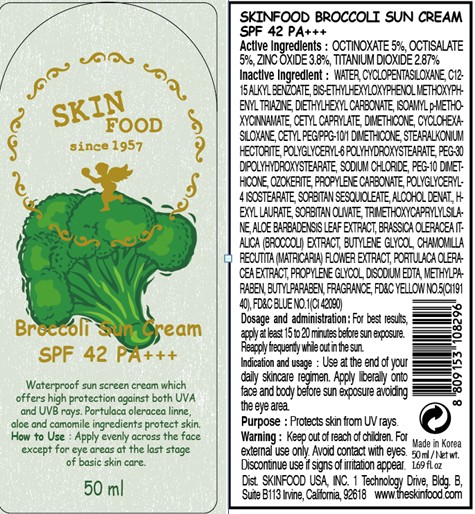 DRUG LABEL: BROCCOLI SUN
NDC: 76214-018 | Form: CREAM
Manufacturer: SKINFOOD CO., LTD.
Category: otc | Type: HUMAN OTC DRUG LABEL
Date: 20110908

ACTIVE INGREDIENTS: OCTINOXATE 2.5 mL/50 mL; OCTISALATE 2.5 mL/50 mL; ZINC OXIDE 1.9 mL/50 mL; TITANIUM DIOXIDE 1.44 mL/50 mL
INACTIVE INGREDIENTS: WATER; CYCLOMETHICONE 5; ALKYL (C12-15) BENZOATE; BEMOTRIZINOL; DIETHYLHEXYL CARBONATE; CETYL OCTANOATE; DIMETHICONE; CYCLOMETHICONE 6; PEG-30 DIPOLYHYDROXYSTEARATE; SODIUM CHLORIDE; PROPYLENE CARBONATE; POLYGLYCERYL-4 ISOSTEARATE; SORBITAN SESQUIOLEATE; HEXYL LAURATE; SORBITAN OLIVATE; TRIMETHOXYCAPRYLYLSILANE; METHYLPARABEN; ALOE VERA LEAF; BROCCOLI; BUTYLENE GLYCOL; BUTYLPARABEN; MATRICARIA RECUTITA; PURSLANE; PROPYLENE GLYCOL; EDETATE DISODIUM

Drug Facts

ACTIVE INGREDIENT

Active ingredients: OCTINOXATE 5%, OCTISALATE 5%, ZINC OXIDE 3.8%, TITANIUM DIOXIDE 2.87%

Inactive ingredients:
WATER, CYCLOPENTASILOXANE, C12-15 ALKYL BENZOATE, BIS-ETHYLHEXYLOXYPHENOL METHOXYPHENYL TRIAZINE, DIETHYLHEXYL CARBONATE, ISOAMYL p-METHOXYCINNAMATE, CETYL CAPRYLATE, DIMETHICONE, CYCLOHEXASILOXANE, CETYL PEG/PPG-10/1 DIMETHICONE, STEARALKONIUM HECTORITE, POLYGLYCERYL-6 POLYHYDROXYSTEARATE,
PEG-30 DIPOLYHYDROXYSTEARATE, SODIUM CHLORIDE, PEG-10 DIMETHICONE, OZOKERITE, PROPYLENE CARBONATE, POLYGLYCERYL-4 ISOSTEARATE, SORBITAN SESQUIOLEATE, ALCOHOL DENAT., HEXYL LAURATE, SORBITAN OLIVATE, TRIMETHOXYCAPRYLYLSILANE, DIMETHICONE, ALOE BARBADENSIS LEAF EXTRACT, BRASSICA OLERACEA ITALICA (BROCCOLI) EXTRACT, BUTYLENE GLYCOL, CHAMOMILLA RECUTITA (MATRICARIA) FLOWER EXTRACT, PORTULACA OLERACEA EXTRACT, PROPYLENE GLYCOL, DISODIUM EDTA, METHYLPARABEN, BUTYLPARABEN, FRAGRANCE

Purpose: Protects skin from UV rays.

Warnings:
For external use only. Avoid contact with eyes.
Discontinue use if signs of irritation appear.

Keep out of reach of children:
Keep out of reach of children.

INDICATIONS AND USAGE

Indication and usage: Use at the end of your daily skincare regimen. Apply liberally onto face and body before sun exposure avoiding the eye area.

Dosage and administration:
For best results, apply at least 15 to 20 minutes before sun exposure.
Reapply frequently while out in the sun.